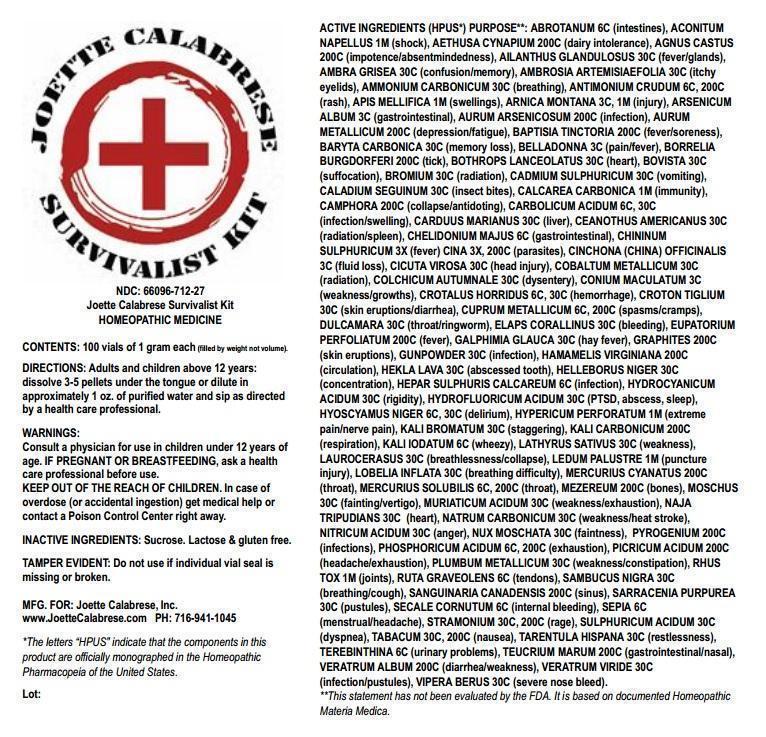 DRUG LABEL: Joette Calabrese Survivalist Kit
NDC: 66096-712 | Form: PELLET
Manufacturer: OHM PHARMA INC.
Category: homeopathic | Type: HUMAN OTC DRUG LABEL
Date: 20211229

ACTIVE INGREDIENTS: ARTEMISIA ABROTANUM FLOWERING TOP 6 [hp_C]/1 1; ACONITUM NAPELLUS 1 [hp_M]/1 1; AETHUSA CYNAPIUM 200 [hp_C]/1 1; CHASTE TREE 200 [hp_C]/1 1; AILANTHUS ALTISSIMA FLOWERING TWIG 30 [hp_C]/1 1; AMBERGRIS 30 [hp_C]/1 1; AMBROSIA ARTEMISIIFOLIA POLLEN 30 [hp_C]/1 1; AMMONIUM CARBONATE 30 [hp_C]/1 1; ANTIMONY TRISULFIDE 6 [hp_C]/1 1; APIS MELLIFERA 1 [hp_M]/1 1; ARNICA MONTANA 3 [hp_C]/1 1; ARSENIC TRIOXIDE 3 [hp_C]/1 1; GOLD 200 [hp_C]/1 1; BAPTISIA TINCTORIA ROOT 200 [hp_C]/1 1; BARIUM CARBONATE 30 [hp_C]/1 1; ATROPA BELLADONNA 3 [hp_C]/1 1; BORRELIA BURGDORFERI 200 [hp_C]/1 1; BOTHROPS ATROX VENOM 30 [hp_C]/1 1; LYCOPERDON UTRIFORME FRUITING BODY 30 [hp_C]/1 1; BROMINE 30 [hp_C]/1 1; CADMIUM SULFATE 30 [hp_C]/1 1; DIEFFENBACHIA SEGUINE 30 [hp_C]/1 1; OYSTER SHELL CALCIUM CARBONATE, CRUDE 1 [hp_M]/1 1; CAMPHOR (NATURAL) 200 [hp_C]/1 1; PHENOL 6 [hp_C]/1 1; MILK THISTLE 30 [hp_C]/1 1; CEANOTHUS AMERICANUS LEAF 30 [hp_C]/1 1; CHELIDONIUM MAJUS 6 [hp_C]/1 1; QUININE SULFATE 3 [hp_X]/1 1; ARTEMISIA CINA PRE-FLOWERING TOP 3 [hp_X]/1 1; CINCHONA OFFICINALIS BARK 3 [hp_C]/1 1; CICUTA VIROSA ROOT 30 [hp_C]/1 1; COBALT 30 [hp_C]/1 1; COLCHICUM AUTUMNALE BULB 30 [hp_C]/1 1; CONIUM MACULATUM FLOWERING TOP 3 [hp_C]/1 1; CROTALUS HORRIDUS HORRIDUS VENOM 6 [hp_C]/1 1; CROTON TIGLIUM SEED 30 [hp_C]/1 1; COPPER 6 [hp_C]/1 1; SOLANUM DULCAMARA TOP 30 [hp_C]/1 1; MICRURUS CORALLINUS VENOM 30 [hp_C]/1 1; EUPATORIUM PERFOLIATUM FLOWERING TOP 200 [hp_C]/1 1; HYDROFLUORIC ACID 30 [hp_C]/1 1; GALPHIMIA GLAUCA FLOWERING TOP 30 [hp_C]/1 1; GRAPHITE 200 [hp_C]/1 1; HAMAMELIS VIRGINIANA ROOT BARK/STEM BARK 200 [hp_C]/1 1; HEKLA LAVA 30 [hp_C]/1 1; HELLEBORUS NIGER ROOT 30 [hp_C]/1 1; CALCIUM SULFIDE 6 [hp_C]/1 1; HYDROGEN CYANIDE 30 [hp_C]/1 1; HYOSCYAMUS NIGER 6 [hp_C]/1 1; HYPERICUM PERFORATUM 1 [hp_M]/1 1; POTASSIUM BROMIDE 30 [hp_C]/1 1; POTASSIUM CARBONATE 200 [hp_C]/1 1; POTASSIUM IODIDE 6 [hp_C]/1 1; LATHYRUS SATIVAS SEED 30 [hp_C]/1 1; PRUNUS LAUROCERASUS LEAF 30 [hp_C]/1 1; LEDUM PALUSTRE TWIG 1 [hp_M]/1 1; LOBELIA INFLATA 30 [hp_C]/1 1; MERCURIC CYANIDE 200 [hp_C]/1 1; MERCURIUS SOLUBILIS 6 [hp_C]/1 1; DAPHNE MEZEREUM BARK 200 [hp_C]/1 1; MOSCHUS MOSCHIFERUS WHOLE 30 [hp_C]/1 1; HYDROCHLORIC ACID 30 [hp_C]/1 1; NAJA NAJA VENOM 30 [hp_C]/1 1; SODIUM CARBONATE 30 [hp_C]/1 1; NITRIC ACID 30 [hp_C]/1 1; NUTMEG 30 [hp_C]/1 1; RANCID BEEF 200 [hp_C]/1 1; PHOSPHORIC ACID 6 [hp_C]/1 1; PICRIC ACID 200 [hp_C]/1 1; LEAD 30 [hp_C]/1 1; TOXICODENDRON PUBESCENS LEAF 1 [hp_M]/1 1; RUTA GRAVEOLENS FLOWERING TOP 6 [hp_C]/1 1; SAMBUCUS NIGRA FLOWERING TOP 30 [hp_C]/1 1; SANGUINARIA CANADENSIS ROOT 200 [hp_C]/1 1; SARRACENIA PURPUREA 30 [hp_C]/1 1; CLAVICEPS PURPUREA SCLEROTIUM 6 [hp_C]/1 1; SEPIA OFFICINALIS JUICE 6 [hp_C]/1 1; DATURA STRAMONIUM 30 [hp_C]/1 1; SULFURIC ACID 30 [hp_C]/1 1; TOBACCO LEAF 30 [hp_C]/1 1; LYCOSA TARANTULA 30 [hp_C]/1 1; TURPENTINE OIL 6 [hp_C]/1 1; TEUCRIUM MARUM 200 [hp_C]/1 1; VERATRUM ALBUM ROOT 200 [hp_C]/1 1; VERATRUM VIRIDE ROOT 30 [hp_C]/1 1; VIPERA BERUS VENOM 30 [hp_C]/1 1
INACTIVE INGREDIENTS: SUCROSE

Joette Calabrese Survivalist Kit

ACTIVE INGREDIENT

ACTIVE INGREDIENTS (HPUS*) PURPOSE**: ABROTANUM 6C (intestines), ACONITUM NAPELLUS 1M (shock), AETHUSA CYNAPIUM 200C (dairy intolerance), AGNUS CASTUS 200C (impotence/absentmindedness), AILANTHUS GLANDULOSUS 30C (fever/glands), AMBRA GRISEA 30C (confusion/memory), AMBROSIA ARTEMISIAEFOLIA 30C (itchy eyelids), AMMONIUM CARBONICUM 30C (breathing), ANTIMONIUM CRUDUM 6C, 200C (rash), APIS MELLIFICA 1M (swellings), ARNICA MONTANA 3C, 1M (injury), ARSENICUM ALBUM 3C (gastrointestinal), AURUM ARSENICOSUM 200C (infection), AURUM METALLICUM 200C (depression/fatigue), BAPTISIA TINCTORIA 200C (fever/soreness), BARYTA CARBONICA 30C (memory loss), BELLADONNA 3C (pain/fever), BORRELIA BURGDORFERI 200C (tick), BOTHROPS LANCEOLATUS 30C (heart), BOVISTA 30C (suffocation), BROMIUM 30C (radiation), CADMIUM SULPHURICUM 30C (vomiting), CALADIUM SEGUINUM 30C (insect bites), CALCAREA CARBONICA 1M (immunity), CAMPHORA 200C (collapse/antidoting), CARBOLICUM ACIDUM 6C, 30C (infection/swelling), CARDUUS MARIANUS 30C (liver), CEANOTHUS AMERICANUS 30C (radiation/spleen), CHELIDONIUM MAJUS 6C (gastrointestinal), CHININUM SULPHURICUM 3X (fever) CINA 3X, 200C (parasites), CINCHONA (CHINA) OFFICINALIS 3C (fluid loss), CICUTA VIROSA 30C (head injury), COBALTUM METALLICUM 30C (radiation), COLCHICUM AUTUMNALE 30C (dysentery), CONIUM MACULATUM 3C (weakness/growths), CROTALUS HORRIDUS 6C, 30C (hemorrhage), CROTON TIGLIUM 30C (skin eruptions/diarrhea), CUPRUM METALLICUM 6C, 200C (spasms/cramps), DULCAMARA 30C (throat/ringworm), ELAPS CORALLINUS 30C (bleeding), EUPATORIUM PERFOLIATUM 200C (fever), GALPHIMIA GLAUCA 30C (hay fever), GRAPHITES 200C (skin eruptions), GUNPOWDER 30C (infection), HAMAMELIS VIRGINIANA 200C (circulation), HEKLA LAVA 30C (abscessed tooth), HELLEBORUS NIGER 30C (concentration), HEPAR SULPHURIS CALCAREUM 6C (infection), HYDROCYANICUM ACIDUM 30C (rigidity), HYDROFLUORICUM ACIDUM 30C (PTSD, abscess, sleep), HYOSCYAMUS NIGER 6C, 30C (delirium), HYPERICUM PERFORATUM 1M (extreme pain/nerve pain), KALI BROMATUM 30C (staggering), KALI CARBONICUM 200C (respiration), KALI IODATUM 6C (wheezy), LATHYRUS SATIVUS 30C (weakness), LAUROCERASUS 30C (breathlessness/collapse), LEDUM PALUSTRE 1M (puncture injury), LOBELIA INFLATA 30C (breathing difficulty), MERCURIUS CYANATUS 200C (throat), MERCURIUS SOLUBILIS 6C, 200C (throat), MEZEREUM 200C (bones), MOSCHUS 30C (fainting/vertigo), MURIATICUM ACIDUM 30C (weakness/exhaustion), NAJA TRIPUDIANS 30C (heart), NATRUM CARBONICUM 30C (weakness/heat stroke), NITRICUM ACIDUM 30C (anger), NUX MOSCHATA 30C (faintness), PYROGENIUM 200C (infections), PHOSPHORICUM ACIDUM 6C, 200C (exhaustion), PICRICUM ACIDUM 200C (headache/exhaustion), PLUMBUM METALLICUM 30C (weakness/constipation), RHUS TOX 1M (joints), RUTA GRAVEOLENS 6C (tendons), SAMBUCUS NIGRA 30C (breathing/cough), SANGUINARIA CANADENSIS 200C (sinus), SARRACENIA PURPUREA 30C (pustules), SECALE CORNUTUM 6C (internal bleeding), SEPIA 6C (menstrual/headache), STRAMONIUM 30C, 200C (rage), SULPHURICUM ACIDUM 30C (dyspnea), TABACUM 30C, 200C (nausea), TARENTULA HISPANA 30C (restlessness), TEREBINTHINA 6C (urinary problems), TEUCRIUM MARUM 200C (gastrointestinal/nasal), VERATRUM ALBUM 200C (diarrhea/weakness), VERATRUM VIRIDE 30C (infection/pustules), VIPERA BERUS 30C (severe nose bleed).

OTHER SAFETY INFORMATION

*The letters “HPUS” indicate that the components in this product are officially monographed in the Homeopathic Pharmacopeia of the United States.
**This statement has not been evaluated by the FDA. It is based on documented Homeopathic Materia Medica.

INDICATIONS AND USAGE

ACTIVE INGREDIENTS (HPUS*) PURPOSE**: ABROTANUM 6C (intestines), ACONITUM NAPELLUS 1M (shock), AETHUSA CYNAPIUM 200C (dairy intolerance), AGNUS CASTUS 200C (impotence/absentmindedness), AILANTHUS GLANDULOSUS 30C (fever/glands), AMBRA GRISEA 30C (confusion/memory), AMBROSIA ARTEMISIAEFOLIA 30C (itchy eyelids), AMMONIUM CARBONICUM 30C (breathing), ANTIMONIUM CRUDUM 6C, 200C (rash), APIS MELLIFICA 1M (swellings), ARNICA MONTANA 3C, 1M (injury), ARSENICUM ALBUM 3C (gastrointestinal), AURUM ARSENICOSUM 200C (infection), AURUM METALLICUM 200C (depression/fatigue), BAPTISIA TINCTORIA 200C (fever/soreness), BARYTA CARBONICA 30C (memory loss), BELLADONNA 3C (pain/fever), BORRELIA BURGDORFERI 200C (tick), BOTHROPS LANCEOLATUS 30C (heart), BOVISTA 30C (suffocation), BROMIUM 30C (radiation), CADMIUM SULPHURICUM 30C (vomiting), CALADIUM SEGUINUM 30C (insect bites), CALCAREA CARBONICA 1M (immunity), CAMPHORA 200C (collapse/antidoting), CARBOLICUM ACIDUM 6C, 30C (infection/swelling), CARDUUS MARIANUS 30C (liver), CEANOTHUS AMERICANUS 30C (radiation/spleen), CHELIDONIUM MAJUS 6C (gastrointestinal), CHININUM SULPHURICUM 3X (fever) CINA 3X, 200C (parasites), CINCHONA (CHINA) OFFICINALIS 3C (fluid loss), CICUTA VIROSA 30C (head injury), COBALTUM METALLICUM 30C (radiation), COLCHICUM AUTUMNALE 30C (dysentery), CONIUM MACULATUM 3C (weakness/growths), CROTALUS HORRIDUS 6C, 30C (hemorrhage), CROTON TIGLIUM 30C (skin eruptions/diarrhea), CUPRUM METALLICUM 6C, 200C (spasms/cramps), DULCAMARA 30C (throat/ringworm), ELAPS CORALLINUS 30C (bleeding), EUPATORIUM PERFOLIATUM 200C (fever), GALPHIMIA GLAUCA 30C (hay fever), GRAPHITES 200C (skin eruptions), GUNPOWDER 30C (infection), HAMAMELIS VIRGINIANA 200C (circulation), HEKLA LAVA 30C (abscessed tooth), HELLEBORUS NIGER 30C (concentration), HEPAR SULPHURIS CALCAREUM 6C (infection), HYDROCYANICUM ACIDUM 30C (rigidity), HYDROFLUORICUM ACIDUM 30C (PTSD, abscess, sleep), HYOSCYAMUS NIGER 6C, 30C (delirium), HYPERICUM PERFORATUM 1M (extreme pain/nerve pain), KALI BROMATUM 30C (staggering), KALI CARBONICUM 200C (respiration), KALI IODATUM 6C (wheezy), LATHYRUS SATIVUS 30C (weakness), LAUROCERASUS 30C (breathlessness/collapse), LEDUM PALUSTRE 1M (puncture injury), LOBELIA INFLATA 30C (breathing difficulty), MERCURIUS CYANATUS 200C (throat), MERCURIUS SOLUBILIS 6C, 200C (throat), MEZEREUM 200C (bones), MOSCHUS 30C (fainting/vertigo), MURIATICUM ACIDUM 30C (weakness/exhaustion), NAJA TRIPUDIANS 30C (heart), NATRUM CARBONICUM 30C (weakness/heat stroke), NITRICUM ACIDUM 30C (anger), NUX MOSCHATA 30C (faintness), PYROGENIUM 200C (infections), PHOSPHORICUM ACIDUM 6C, 200C (exhaustion), PICRICUM ACIDUM 200C (headache/exhaustion), PLUMBUM METALLICUM 30C (weakness/constipation), RHUS TOX 1M (joints), RUTA GRAVEOLENS 6C (tendons), SAMBUCUS NIGRA 30C (breathing/cough), SANGUINARIA CANADENSIS 200C (sinus), SARRACENIA PURPUREA 30C (pustules), SECALE CORNUTUM 6C (internal bleeding), SEPIA 6C (menstrual/headache), STRAMONIUM 30C, 200C (rage), SULPHURICUM ACIDUM 30C (dyspnea), TABACUM 30C, 200C (nausea), TARENTULA HISPANA 30C (restlessness), TEREBINTHINA 6C (urinary problems), TEUCRIUM MARUM 200C (gastrointestinal/nasal), VERATRUM ALBUM 200C (diarrhea/weakness), VERATRUM VIRIDE 30C (infection/pustules), VIPERA BERUS 30C (severe nose bleed).

WARNINGS:
Consult a physician for use in children under 12 years of age. IF PREGNANT OR BREASTFEEDING, ask a health care professional before use.
In case of overdose (or accidental ingestion) get medical help or contact a Poison Control Center right away.

KEEP OUT OF THE REACH OF CHILDREN.

DOSAGE AND ADMINISTRATION

DIRECTIONS: Adults and children above 12 years: dissolve 3-5 pellets under the tongue or dilute in approximately 1 oz of purified water and sip as directed by a health care professional.

OTHER SAFETY INFORMATION

TAMPER EVIDENT: Do not use if individual vial seal is missing or broken.

INACTIVE INGREDIENTS: Sucrose. Lactose and gluten free.

QUESTIONS

MFG. FOR: Joette Calabrese, Inc.
www.JoetteCalabrese.com
PH: 716-941-1045

PACKAGE LABEL

NDC: 66096-712-27
Joette Calabrese Survivalist Kit
HOMEOPATHIC MEDICINE
CONTENTS: 100 vials of 1 gram each (filled by weight not volume).